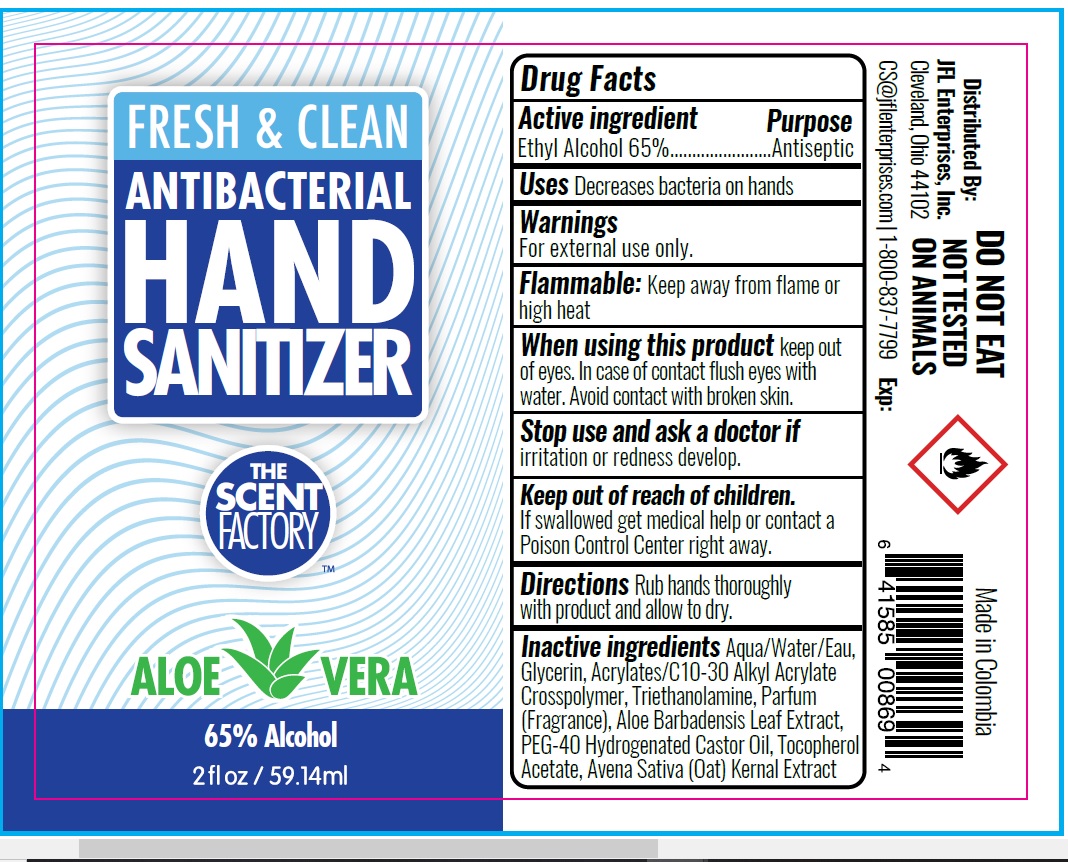 DRUG LABEL: Fresh and Clean Hand Sanitizer
NDC: 71246-0013 | Form: GEL
Manufacturer: JFL Enterprises, Inc.
Category: otc | Type: HUMAN OTC DRUG LABEL
Date: 20200709

ACTIVE INGREDIENTS: ALCOHOL 650 mL/1000 mL
INACTIVE INGREDIENTS: CARBOMER INTERPOLYMER TYPE A (ALLYL SUCROSE CROSSLINKED); WATER; GLYCERIN; TROLAMINE; OAT; ALOE VERA LEAF; POLYOXYL 40 HYDROGENATED CASTOR OIL; .ALPHA.-TOCOPHEROL ACETATE

The Scent Factory - Fresh & Clean Antibacterial Hand Sanitizer

Active Ingredient - Ethyl Alcohol 65%.....Antiseptic

Purpose - Antiseptic

Use

To decrease bacteria on hands

Warnings

For external use only

Flammable, keep away from fire or flame

Keep out of reach of children

If accidently swallowed, get medical help or contact a Poison Control Center right away

WHEN USING SECTION

Keep out of eyes,In case of contact flush eyes with water.

Avoid contact with broken skin.

ASK DOCTOR

Discontinue use if irritation or redness develop.

Directions

- Rub hands thoroughly with product and allow to dry.

Inactive Ingredients

Water, Glycerin, Acrylates/C10-30 Alkyl Acrylate Crosspolymer, Triethanolamine, Parfum ,Aloe bardadensis Leaf Extract,

PEG-40 Hydrogenated Castor Oil, Tocopherol Acetate , Avena Sativa(Oat) Kernal Extract.